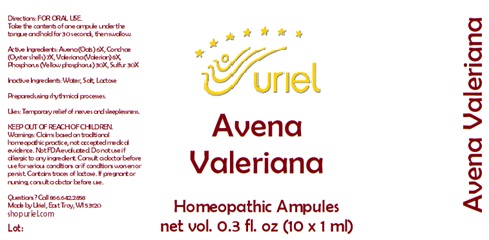 DRUG LABEL: Avena Valeriana
NDC: 48951-1211 | Form: LIQUID
Manufacturer: Uriel Pharmacy Inc.
Category: homeopathic | Type: HUMAN OTC DRUG LABEL
Date: 20251030

ACTIVE INGREDIENTS: AVENA SATIVA FLOWERING TOP 6 [hp_X]/1 mL; OSTREA EDULIS SHELL 7 [hp_X]/1 mL; VALERIAN 8 [hp_X]/1 mL; PHOSPHORUS 30 [hp_X]/1 mL; SULFUR 30 [hp_X]/1 mL
INACTIVE INGREDIENTS: WATER; SODIUM CHLORIDE

Avena Valeriana

INDICATIONS AND USAGE

Directions: FOR ORAL USE.

DOSAGE AND ADMINISTRATION

Take the contents of one ampule under the tongue and hold for 30 seconds, then swallow.

ACTIVE INGREDIENT

Active Ingredients: Avena e pl. tota 6X, Conchae 7X, Valeriana e rad. 8X, Phosphorus 30X, Sulfur 30X

Inactive Ingredients: Water, Salt, Lactose

Prepared using rhythmical processes.

PURPOSE

Uses: Temporary relief of nerves and sleeplessness.

KEEP OUT OF REACH OF CHILDREN.

WARNINGS

Warnings: Claims based on traditional homeopathic practice, not accepted medical evidence. Not FDA evaluated. Do not use if allergic to any ingredient. Consult a doctor before use for serious conditions or if conditions worsen or persist. Contains traces of lactose. If pregnant or nursing, consult a doctor before use.

Questions? Call 866.642.2858
Made by Uriel, East Troy, WI 53120
shopuriel.com